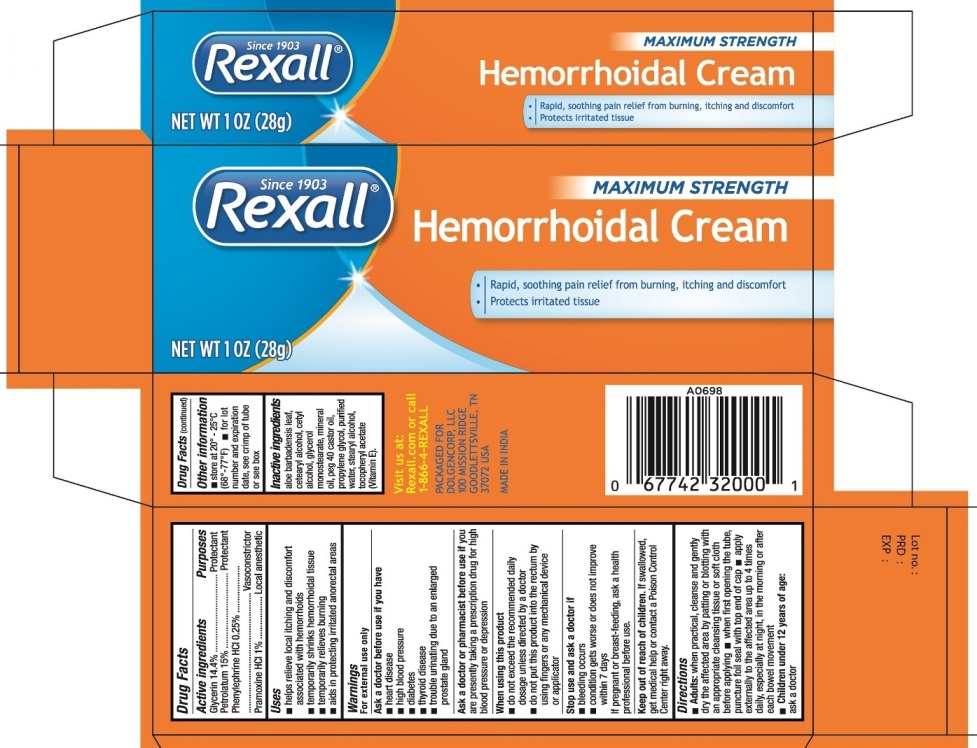 DRUG LABEL: Rexall Maximum Strength Hemorrhoidal
NDC: 55910-406 | Form: CREAM
Manufacturer: Dolgencorp, Inc.
Category: otc | Type: HUMAN OTC DRUG LABEL
Date: 20160701

ACTIVE INGREDIENTS: GLYCERIN 14.4 g/100 g; PETROLATUM 15 g/100 g; PHENYLEPHRINE HYDROCHLORIDE 0.25 g/100 g; PRAMOXINE HYDROCHLORIDE 1 g/100 g
INACTIVE INGREDIENTS: ALOE VERA LEAF; CETOSTEARYL ALCOHOL; CETYL ALCOHOL; GLYCERYL MONOSTEARATE; MINERAL OIL; PEG-40 CASTOR OIL; PROPYLENE GLYCOL; WATER; STEARYL ALCOHOL; .ALPHA.-TOCOPHEROL ACETATE

Rexall Maximum Strength Hemorrhoidal

Active ingredients
Glycerin 14.4%
Petrolatum 15%
Phenylephrine Hydrochloride 0.25%
Pramoxine HCl 1%

Purpose

Protectant
Protectant
Vasoconstrictor
Local anesthetic

Uses

- helps relieve the local itching and discomfort associated with hemorrhoids
- temporarily shrinks hemorrhoidal tissue
- temporary relieves burning
- aid in protecting irritated anorectal areas

Warnings
For external use only.
Ask a doctor before use if you have

- heart disease
- high blood pressure
- diabetes
- thyroid disease
- trouble urinating due to an enlarged prostate gland

Ask a doctor or pharmacist before use if you are presently taking a prescription drug for high blood pressure or depression
When using this product

- do not exceed the recommended daily dosage unless directed by a doctor
- do not put this product into rectum by using fingers or any mechanical device or applicator

Stop use and ask a doctor if

- bleeding occurs
- condition gets worse or does not improve within 7 days

If pregnant or breast-feeding, ask a health professional before use.

Keep out of reach of children. If swallowed, get medical help or contact a Poison Control Center right away.

Directions

- Adults: when practical, cleanse and gently dry the affected area by patting or blotting with an appropriate cleansing tissue or soft cloth before applying.
- when first opening the tube, puncture foil seal with top end of cap.
- apply externally to the affected area up to 4 times daily, especially at night, in the morning or after each bowel movement
- Children under 12 years of age: ask a doctor

Other information

- store at 20°- 25°C (68°- 77°F)
- for lot number and expiration date, see crimp of tube or see box

Inactive ingredients

aloe barbadensis leaf, cetearyl alcohol, cetyl alcohol, glycerol monostearate, mineral oil, peg 40 castor oil, propylene glycol, purified water,
stearyl alcohol, tocopheryl acetate (Vitamin E).

PACKAGE LABEL

PRINCIPAL DISPLAY PANEL

REXALL MAXIMUM STRENGTH HEMORRHOIDAL

NET WT 1 OZ (28 g)